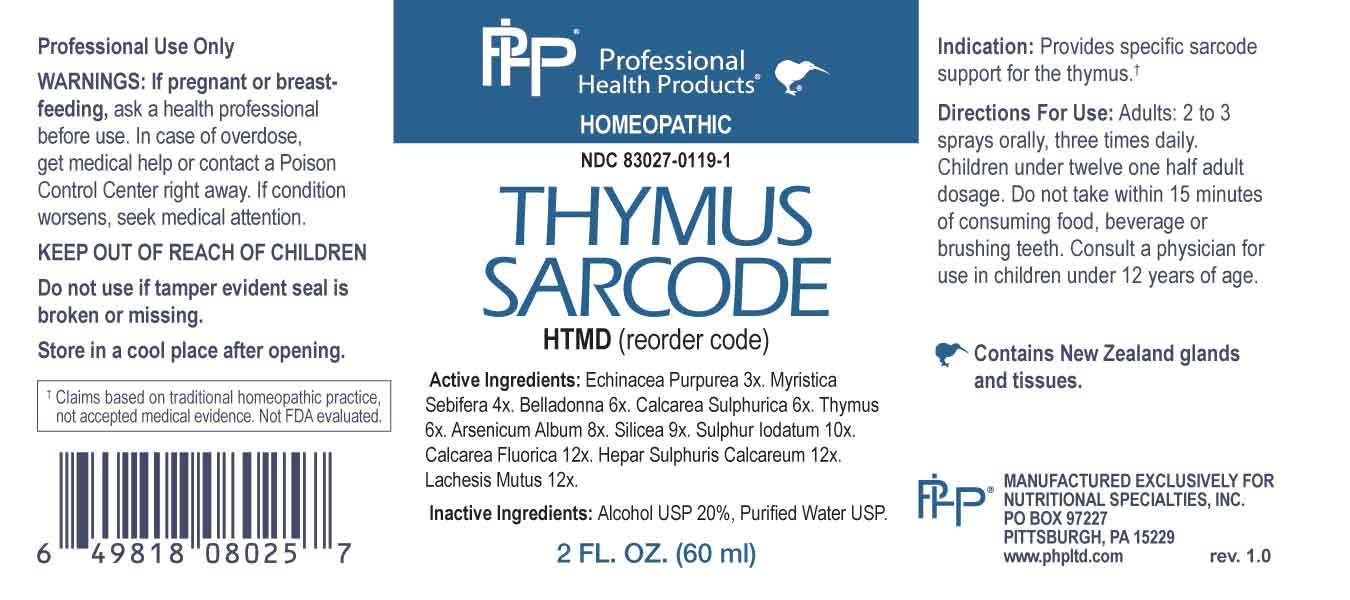 DRUG LABEL: Thymus Sarcode
NDC: 83027-0119 | Form: SPRAY
Manufacturer: Nutritional Specialties, Inc.
Category: homeopathic | Type: HUMAN OTC DRUG LABEL
Date: 20231101

ACTIVE INGREDIENTS: ECHINACEA PURPUREA WHOLE 3 [hp_X]/1 mL; VIROLA SEBIFERA RESIN 4 [hp_X]/1 mL; ATROPA BELLADONNA 6 [hp_X]/1 mL; CALCIUM SULFATE ANHYDROUS 6 [hp_X]/1 mL; LAMB 6 [hp_X]/1 mL; ARSENIC TRIOXIDE 8 [hp_X]/1 mL; SILICON DIOXIDE 9 [hp_X]/1 mL; SULFUR IODIDE 10 [hp_X]/1 mL; CALCIUM FLUORIDE 12 [hp_X]/1 mL; CALCIUM SULFIDE 121 [hp_X]/1 mL; LACHESIS MUTA VENOM 12 [hp_X]/1 mL
INACTIVE INGREDIENTS: WATER; ALCOHOL

DRUG FACTS:

ACTIVE INGREDIENTS:

Echinacea Purpurea 3X, Myristica Sebifera 4X, Belladonna 6X, Calcarea Sulphurica 6X, Thymus 6X, Arsenicum Album 8X, Silicea 9X, Sulphur Iodatum 10X, Calcarea Fluorica 12X, Hepar Sulphuris Calcareum 12X, Lachesis Mutus 12X.

PURPOSE:

Provides specific sarcode support for the thymus†

†Claims based on traditional homeopathic practice, not accepted medical evidence. Not FDA evaluated.

WARNINGS:

Professional Use Only

If pregnant or breast-feeding, ask a health professional before use.

In case of overdose, get medical help or contact a Poison Control Center right away.

If condition worsens, seek medical attention.

KEEP OUT OF REACH OF CHILDREN

Do not use if tamper evident seal is broken or missing.

Store in a cool place after opening

KEEP OUT OF REACH OF CHILDREN:

In case of overdose, get medical help or contact a Poison Control Center right away.

DIRECTIONS:

Adults: 2 to 3 sprays orally, three times daily. Children under twelve one half adult dosage. Do not take within 15 minutes of consuming food, beverage or brushing teeth. Consult a physician for use in children under 12 years of age.

INDICATIONS:

Provides specific sarcode support for the fthymus†

†Claims based on traditional homeopathic practice, not accepted medical evidence. Not FDA evaluated.

INACTIVE INGREDIENTS:

Alcohol USP 20%, Purified Water USP.

QUESTIONS:

MANUFACTURED EXCLUSIVELY FOR

NUTRITIONAL SPECIALTIES, INC.

PO BOX 97227

PITTSBURG, PA 15229

www.phpltd.com

PACKAGE LABEL DISPLAY:

Professional

Health Products

HOMEOPATHIC

NDC 83027-0119-1

THYMUS SARCODE

2 FL. OZ (60 ml)